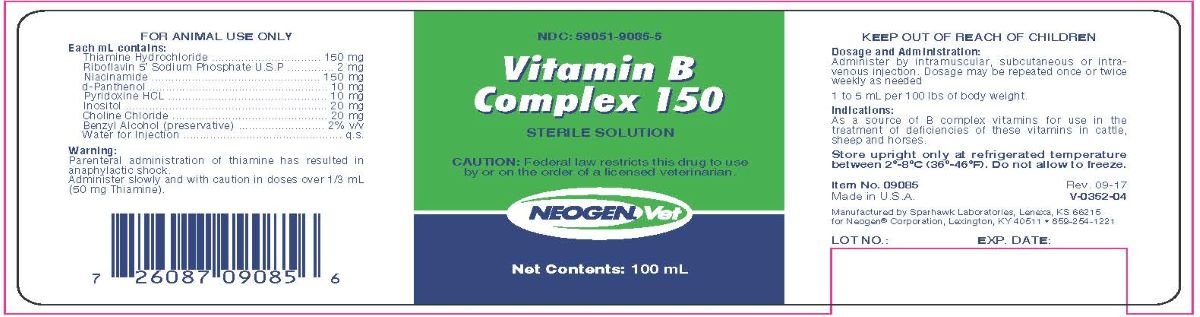 DRUG LABEL: Vitamin B Complex 150
NDC: 59051-9085 | Form: INJECTION
Manufacturer: Neogen Corporation - Nandino
Category: animal | Type: PRESCRIPTION ANIMAL DRUG LABEL
Date: 20231218

ACTIVE INGREDIENTS: THIAMINE HYDROCHLORIDE 150 mg/1 mL; RIBOFLAVIN 5'-PHOSPHATE SODIUM 2 mg/1 mL; NIACINAMIDE 150 mg/1 mL; PANTHENOL 10 mg/1 mL; PYRIDOXINE HYDROCHLORIDE 10 mg/1 mL; INOSITOL 20 mg/1 mL; CHOLINE CHLORIDE 20 mg/1 mL
INACTIVE INGREDIENTS: BENZYL ALCOHOL .02 mL/1 mL; WATER

Vitamin B Complex 150
Sterile Solution

Indications:

As a source of B complex vitamins for use in the treatment of deficiencies of these vitamins in cattle, sheep and horses.

Each mL Contains:

Thiamine Hydrochloride..................................................150 mg

Riboflavin 5' Sodium Phosphate USP....................................2 mg

Niacinamide..................................................................150 mg

d-Panthenol....................................................................10 mg

Pyridoxine HCL................................................................10 mg

Inositol..........................................................................20 mg

Choline Chloride..............................................................20 mg

Benzyl Alcohol (preservative)...........................................2% v/v

Water for Injection...............................................................q.s.

Dosage and Administration:

Administer by intramuscular or intravenous injection. Dosage may be repeated once or twice weekly as needed.

1 to 5 mL per 100 lbs of body weight.

Warning:

Parenteral administration of thiamine has resulted in anaphylactic shock. Administer slowly and with caution in doses
over 1/3 mL (50 mg Thiamine).

STORAGE AND HANDLING

Store upright only at refrigerated temperature between 2º-8ºC (36º-46ºF). Do not allow to freeze.

Manufactured by Sparhawk Laboratories, Lenexa, KS 66215 for Neogen® Corporation, Lexington, KY 40511 • 859-254-1221

Item No. 09085

Made in USA

Rev. 09-17

V-0352-04

Lot No.:

Exp. Date

Principal Display Panel

NDC: 59051-9085-5

Vitamin B

complex 150

sterile solution

Caution: Federal law restricts this drug to use by or on the order of a licensed veterinarian

FOR ANIMAL USE ONLY

KEEP OUT OF THE REACH OF CHILDREN

Net Content: 100 mL